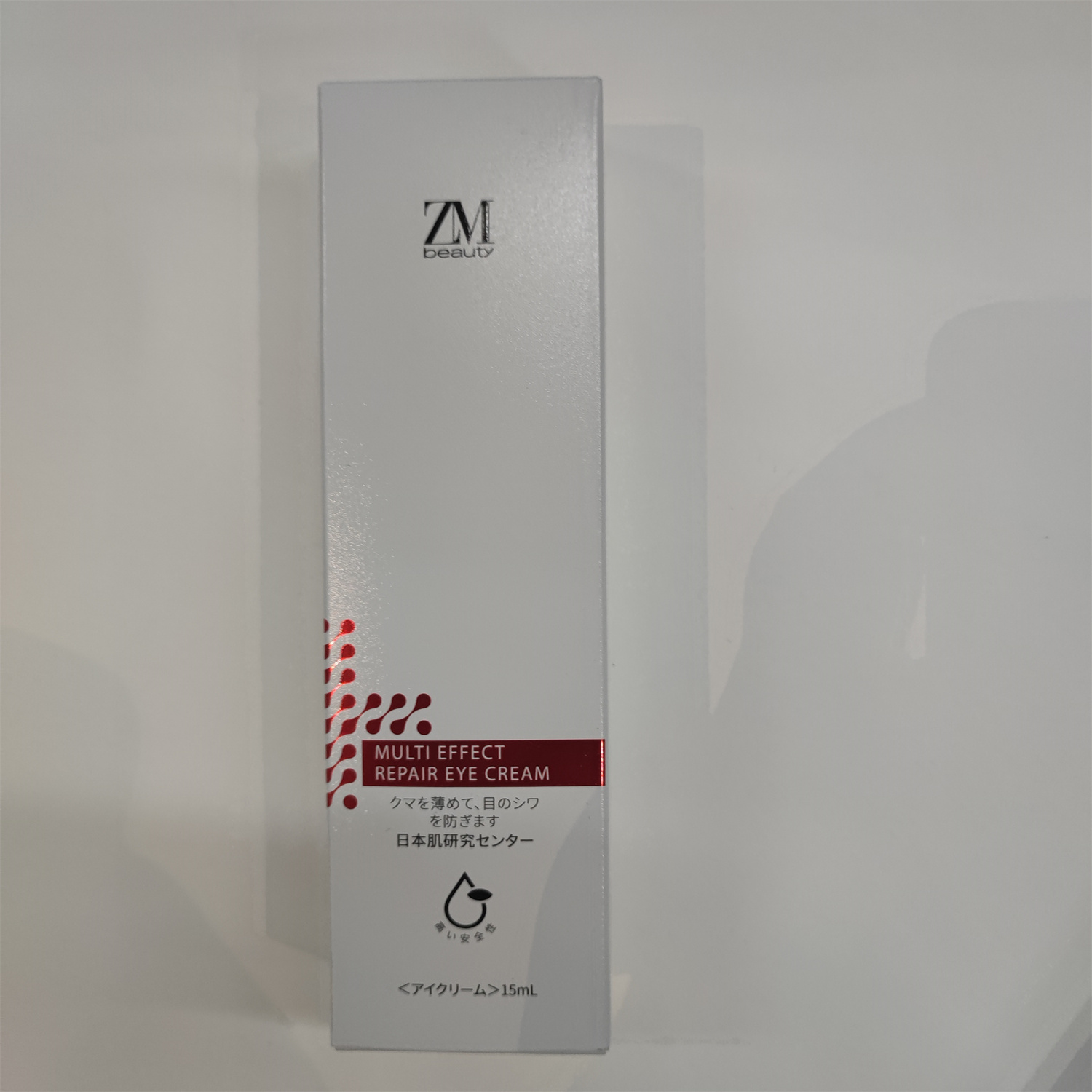 DRUG LABEL: multi effect repair cream
NDC: 84716-005 | Form: OINTMENT
Manufacturer: Shenzhen Boyang E-commerce Co.
Category: otc | Type: HUMAN OTC DRUG LABEL
Date: 20241014

ACTIVE INGREDIENTS: BUTYLENE GLYCOL 1.425 g/15 mL; SQUALANE 0.9 g/15 mL; PENTYLENE GLYCOL 0.75 g/15 mL
INACTIVE INGREDIENTS: WATER 9.6375 mL/15 mL

ACTIVE INGREDIENTS

BUTYLENE GLYCOL 9.5%
SQUALANE 6%
PENTYLENE GLYCOL 5%

PURPOSE

Reduces dark circles and prevents eye wrinkles

USES

Use daily in the morning and evening after cleansing, together with lotion to tone the skin. Take the beauty solution on your fingertips and apply an appropriate amount to the areas with wrinkles.
For each 1 area (including crow's feet of both eyes, wrinkles on both cheeks, forehead, etc.), use about 2 grains of rice.

Warnings

Please place it out of the reach of infants; lt is recommended to have a skin test (inside the wrist or behind the ear) before use.lf you feel uncomfortable,please stop using it.

Stop use and ask a doctor if

lt is recommended to have a skin test (inside the wrist orbehind the ear) before use.If you feel uncomfortable,please stop using it.

Do not use

on damaged or broken skin

Keep out of reach of children

Please place it out of the reach of infants；If swallowed, get medical help or contact a Poison Control Center right away.

When using this product

For external use only

keep out of eyes. Rinse with water to remove.

INACTIVE INGREDIENT SECTON

water

uses and storage method

USES：

Use daily in the morning and evening after cleansing, together with lotion to tone the skin. Take the beauty solution on your fingertips and apply an appropriate amount to the areas with wrinkles.
For each 1 area (including crow's feet of both eyes, wrinkles on both cheeks, forehead, etc.), use about 2 grains of rice.

Please place it out of the reach of infants

For external use only

keep out of eyes. Rinse with water to remove.